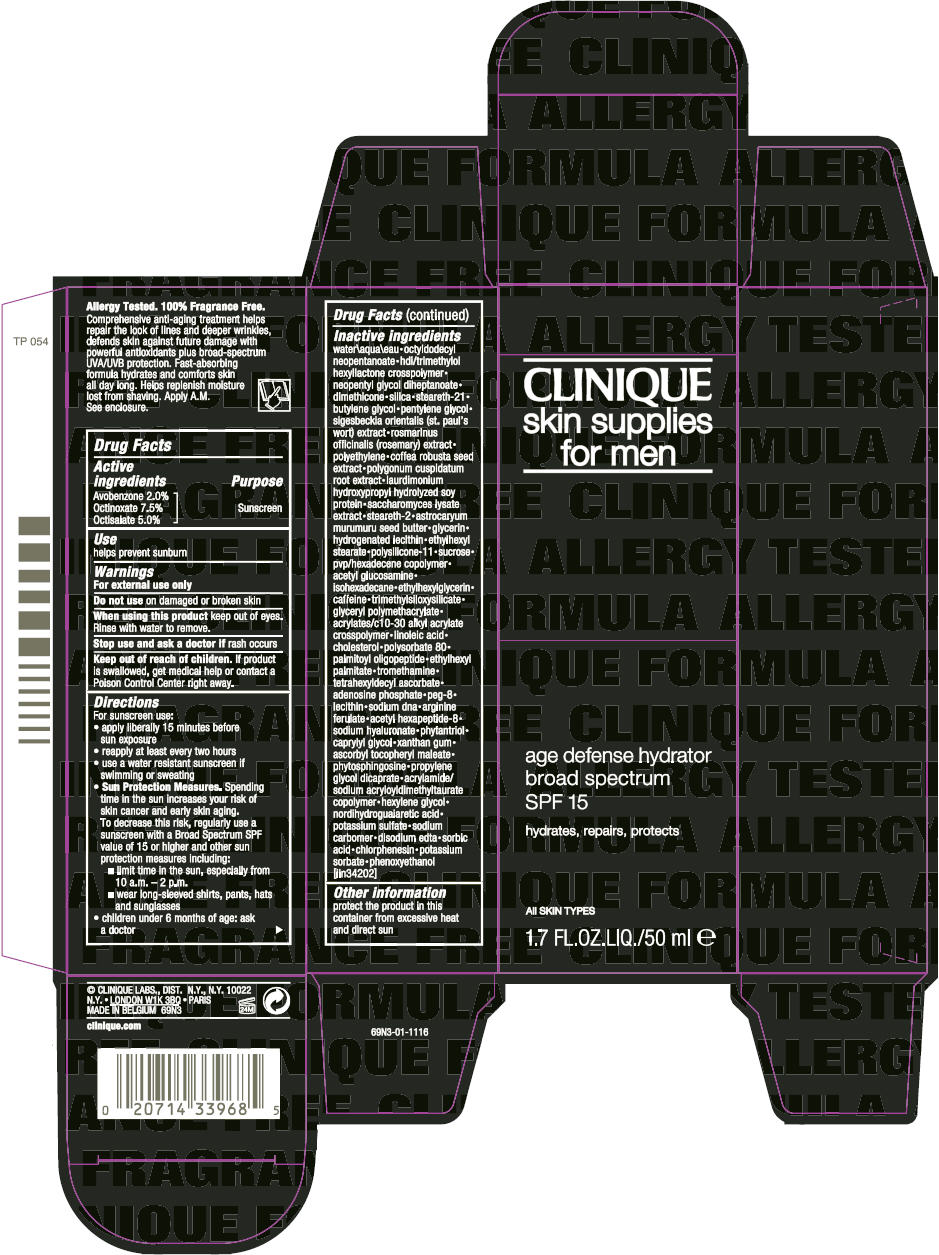 DRUG LABEL: CLINIQUE 
NDC: 49527-035 | Form: LIQUID
Manufacturer: CLINIQUE  LABORATORIES INC.
Category: otc | Type: HUMAN OTC DRUG LABEL
Date: 20130605

ACTIVE INGREDIENTS: AVOBENZONE 0.0203 g/1 mL; OCTINOXATE 0.076 g/1 mL; OCTISALATE 0.0507 g/1 mL
INACTIVE INGREDIENTS: water; octyldodecyl neopentanoate; neopentyl glycol diheptanoate; dimethicone; silicon dioxide; steareth-21; butylene glycol; pentylene glycol; rosemary; high density polyethylene; robusta coffee bean; polygonum cuspidatum root; saccharomyces lysate; steareth-2; astrocaryum murumuru seed butter; glycerin; ethylhexyl stearate; sucrose; n-acetylglucosamine; isohexadecane; ethylhexylglycerin; caffeine; linoleic acid; cholesterol; polysorbate 80; palmitoyl oligopeptide; ethylhexyl palmitate; tromethamine; tetrahexyldecyl ascorbate; adenosine phosphate; polyethylene glycol 400; acetyl hexapeptide-8; hyaluronate sodium; phytantriol; caprylyl glycol; xanthan gum; ascorbyl tocopheryl maleate; phytosphingosine; propylene glycol dicaprate; hexylene glycol; masoprocol; potassium sulfate; edetate disodium; sorbic acid; chlorphenesin; potassium sorbate; phenoxyethanol

CLINIQUE
SKIN SUPPLIES FOR MEN AGE DEFENSE HYDRATOR BROAD SPECTRUM SPF 15

Drug Facts

Active ingredients

Avobenzone 2.0%
Octinoxate 7.5%
Octisalate 5.0%

Purpose

Sunscreen

Use

helps prevent sunburn

Warnings

For external use only

Do not use on damaged or broken skin

When using this product keep out of eyes. Rinse with water to remove.

Stop use and ask a doctor if rash occurs

Keep out of reach of children. If product is swallowed, get medical help or contact a Poison Control Center right away.

Directions

For sunscreen use:

- apply liberally 15 minutes before sun exposure
- reapply at least every two hours
- use a water resistant sunscreen if swimming or sweating
- Sun Protection Measures. Spending time in the sun increases your risk of skin cancer and early skin aging. To decrease this risk, regularly use a sunscreen with Broad Spectrum SPF value of 15 or higher and other sun protection measures including:
  - limit time in the sun, especially from 10 a.m. – 2 p.m.
  - wear long-sleeved shirts, pants, hats and sunglasses
- children under 6 months of age: ask a doctor

Inactive ingredients

water\aqua\eau • octyldodecyl neopentanoate • hdi/trimethylol hexyllactone crosspolymer • neopentyl glycol diheptanoate • dimethicone • silica • steareth-21 • butylene glycol • pentylene glycol • sigesbeckia orientalis (st. paul's wort) extract • rosmarinus officinalis (rosemary) extract • polyethylene • coffea robusta seed extract • polygonum cuspidatum root extract • laurdimonium hydroxypropyl hydrolyzed soy protein • saccharomyces lysate extract • steareth-2 • astrocaryum murumuru seed butter • glycerin • hydrogenated lecithin • ethylhexyl stearate • polysilicone-11 • sucrose • pvp/hexadecene copolymer • acetyl glucosamine • isohexadecane • ethylhexylglycerin • caffeine • trimethylsiloxysilicate • glyceryl polymethacrylate • acrylates/c10-30 alkyl acrylate crosspolymer • linoleic acid • cholesterol • polysorbate 80 • palmitoyl oligopeptide • ethylhexyl palmitate • tromethamine • tetrahexyldecyl ascorbate • adenosine phosphate • peg-8 • lecithin • sodium dna • arginine ferulate • acetyl hexapeptide-8 • sodium hyaluronate • phytantriol • caprylyl glycol • xanthan gum • ascorbyl tocopheryl maleate • phytosphingosine • propylene glycol dicaprate • acrylamide/sodium acryloyldimethyltaurate copolymer • hexylene glycol • nordihydroguaiaretic acid • potassium sulfate • sodium carbomer • disodium edta • sorbic acid • chlorphenesin • potassium sorbate • phenoxyethanol [iln34202]

Other information

protect the product in this container from excessive heat and direct sun

PRINCIPAL DISPLAY PANEL - 50 ml Bottle Carton

CLINIQUE
skin supplies
for men

age defense hydrator
broad spectrum
SPF 15

hydrates, repairs, protects

ALL SKIN TYPES

1.7 FL.OZ.LIQ./50 ml e